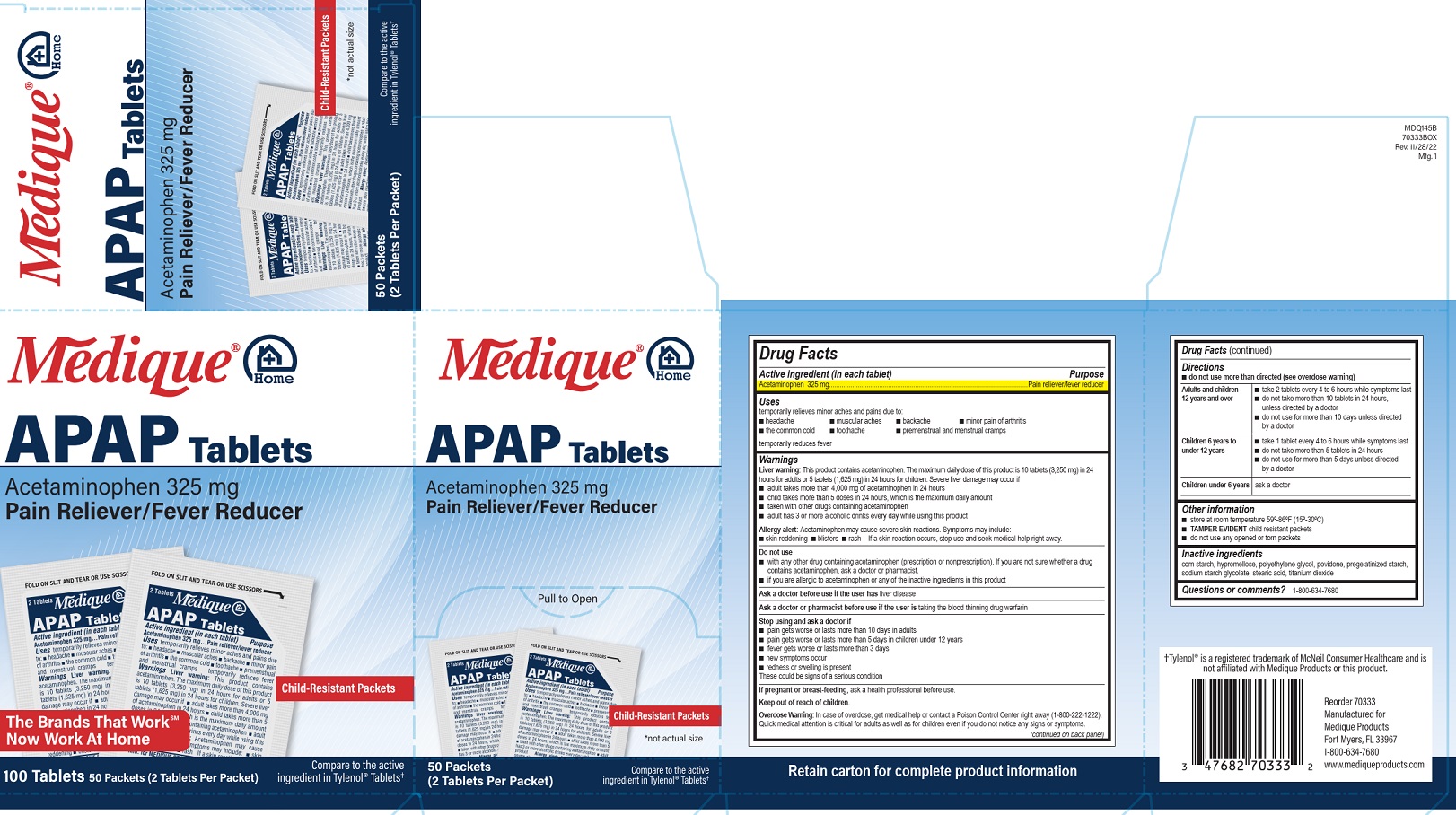 DRUG LABEL: Medique at Home APAP
NDC: 47682-434 | Form: TABLET, COATED
Manufacturer: Unifirst First Aid Corporation
Category: otc | Type: HUMAN OTC DRUG LABEL
Date: 20250908

ACTIVE INGREDIENTS: ACETAMINOPHEN 325 mg/1 1
INACTIVE INGREDIENTS: TITANIUM DIOXIDE; STEARIC ACID; HYPROMELLOSE, UNSPECIFIED; POLYETHYLENE GLYCOL, UNSPECIFIED; SODIUM STARCH GLYCOLATE TYPE A POTATO; STARCH, CORN; POVIDONE

Medique @ Home APAP

Drug Facts

Active ingredient (in each tablet)

Acetaminophen 325 mg.

Purpose

Pain reliever/fever reducer

Uses

temporarily relieves minor aches and pains due to:

■ headache

■ muscular aches

■ backache

■ minor pain of arthritis

■ the common cold

■ toothache

■ premenstrual and menstrual cramps

temporarily reduces fever

Warnings

Liver warning: This product contains acetaminophen. The maximum daily dose of this product is 10 tablets (3,250 mg) in 24 hours for adults or 5 tablets (1,625 mg) in 24 hours for children. Severe liver damage may occur if

■ adult takes more than 4,000 mg of acetaminophen in 24 hours

■ child takes more than 5 doses in 24 hours, which is the maximum daily amount

■ taken with other drugs containing acetaminophen

■ adult has 3 or more alcoholic drinks every day while using this product

Allergy alert: Acetaminophen may cause severe skin reactions. Symptoms may include:

■ skin reddening

■ blisters

■ rash

If a skin reaction occurs, stop use and seek medical help right away.

Do not use

■ with any other drug containing acetaminophen (prescription or nonprescription). If you are not sure whether a
drug contains acetaminophen, ask a doctor or pharmacist.

■ if you are allergic to acetaminophen or any of the inactive ingredients in this product

Ask a doctor before use ifthe user has liver disease

Ask a doctor or pharmacist before use if the user is taking the blood thinning drug warfarin

Stop using and ask a doctor if

■ pain gets worse or lasts more than 10 days in adults

■ pain gets worse or lasts more than 5 days in children under 12 years

■ fever gets worse or lasts more than 3 days

■ new symptoms occur

■ redness or swelling is present

These could be signs of a serious condition.

PREGNANCY OR BREAST FEEDING

If pregnant or breast-feeding, ask a health professional before use.

Keep out of reach of children.

Overdose Warning:

In case of overdose, get medical help or contact a Poison Control Center right away (1-800-222-1222). Quick medical attention is critical for adults as well as for children even if you do not notice any signs or symptoms.

Directions

■ do not use more than directed (see overdose warning)

Adults and children 12 years and over ■ take 2 tablets every 4 to 6 hours while symptoms last
■ do not take more than 10 tablets in 24 hours, unless directed by a doctor ■ do not use for more than 10 days unless directed by a doctor

Children 6 years to under 12 years ■ take 1 tablet every 4 to 6 hours while symptoms last
■ do not take more than 5 tablets in 24 hours ■ do not use for more than 5 days unless directed by a doctor

Children under 6 years ask a doctor

Other information

■ store at room temperature 59º-86ºF (15º-30ºC)

■ TAMPER EVIDENT child resistant packets

■ do not use any opened or torn packets

Inactive ingredients

corn starch, hypromellose, polyethylene glycol, povidone, pregelatinized starch, sodium starch glycolate, stearic acid, titanium dioxide

Questions or comments? 1-800-634-7680

PACKAGE LABEL

Mediqque® @ Home

APAP Tablets

Acetaminophen 325 mg

Pain Reliever/Fever Reducer

Pull to Open

Child-Resistant Packets

*not actual size

50 Packets

(2 Tablets per Packet)

Compare to the active ingredient in Tylenol® Tablets